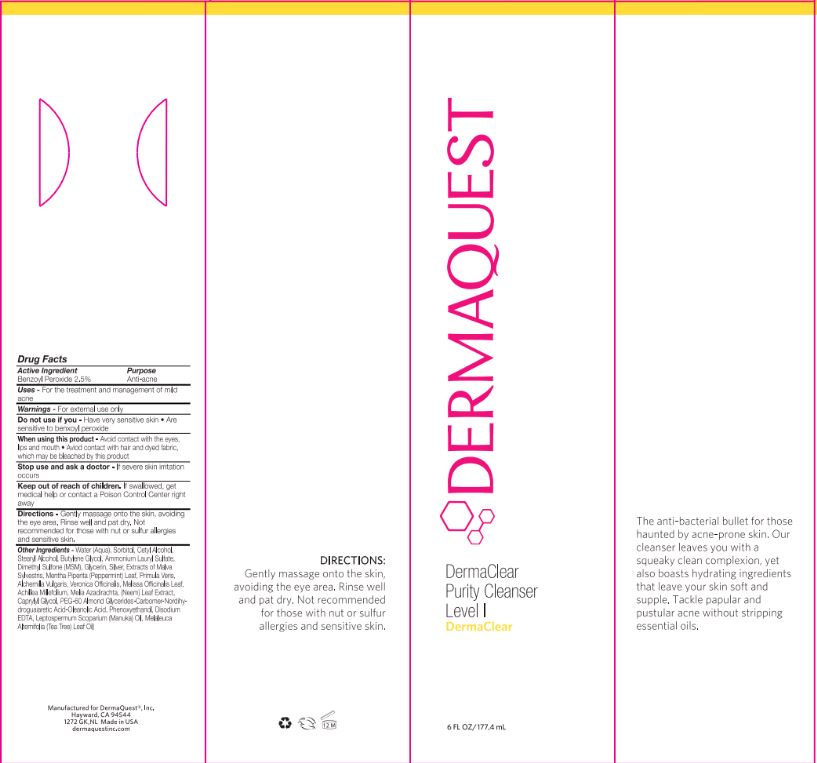 DRUG LABEL: DermaClear Purity Cleanser Level I
NDC: 62742-4092 | Form: GEL
Manufacturer: Allure Labs, Inc.
Category: otc | Type: HUMAN OTC DRUG LABEL
Date: 20171128

ACTIVE INGREDIENTS: BENZOYL PEROXIDE 25 mg/1 mL
INACTIVE INGREDIENTS: WATER; SORBITOL; CETYL ALCOHOL; STEARYL ALCOHOL; PROPYLENE GLYCOL; GLYCERIN; AMMONIUM LAURYL SULFATE; PHENOXYETHANOL; CAPRYLYL GLYCOL; ETHYLHEXYLGLYCERIN; HEXYLENE GLYCOL; DIMETHYL SULFONE; PPG-12/SMDI COPOLYMER; EDETATE DISODIUM; AZADIRACHTA INDICA LEAF; SILVER; TEA TREE OIL; SALIX ALBA BARK; MALVA SYLVESTRIS FLOWERING TOP; MENTHA PIPERITA LEAF; PRIMULA VERIS; ALCHEMILLA XANTHOCHLORA FLOWERING TOP; VERONICA OFFICINALIS FLOWERING TOP; BUTYLENE GLYCOL; PEG-60 ALMOND GLYCERIDES; CARBOMER COPOLYMER TYPE B (ALLYL PENTAERYTHRITOL CROSSLINKED); NORDIHYDROGUAIARETIC ACID, (+/-)-; OLEANOLIC ACID; LEPTOSPERMUM SCOPARIUM LEAF

Drug Facts

Active Ingredient: Benzoyl Peroxide - 2.5%

Purpose: Anti-acne

Uses:

For the treatment and management of mild acne.

Warnings:

For external use only.

Do not use if you:

- Have any sensitive skin.
- Are sensitive to benzoyl peroxide.

When using this product:

- Avoid contact with eyes, lips and mouth.
- Avoid contact with hair and dyed fabric, which may be bleached by this product.

Stop use and ask a doctor - if severe skin irritation occurs.

Keep out of reach of children:

If swallowed, get medical help or contact a Poison Control Center right away.

Directions:

- Emulsify cleanser with lukewarm water and gently massage onto the skin.
- Rinse well and pat dry.
- Not recommended for those with nut allergies.

INACTIVE INGREDIENT

Other Ingredients: Water (Aqua), Sorbitol, Cetyl Alcohol, Stearyl Alcohol, Propylene Glycol, Glycerin, Ammonium Lauryl Sulfate, Phenoxyethanol, Caprylyl Glycol, Ethylhexylglycerin, Hexylene Glycol, Dimethyl Sulfone, PPG-12/SMDI Copolymer, Disodium EDTA, Melia Azadirechta Leaf Extract, Silver, Melaleuca Alternifolia (Tea Tree) Leaf Oil, Salix Alba (Willow) Bark Extract, Malva Sylvestris (Mallow) Extract, Mentha Piperita (Peppermint) Leaf Extract, Achillea Millefoluium Extract, Butylene Glycol, PEG-60 Almond Glycerides, Carbomer, Nordihydroguaiaretic Acid, Oleanolic Acid, Leptospermum Scoparium Branch/Leaf Oil.

PACKAGE LABEL

Manufactured for DermaQuest, Inc.

Hayward, CA 94544

1272 GK, NL Made in USA

dermaquestinc.com